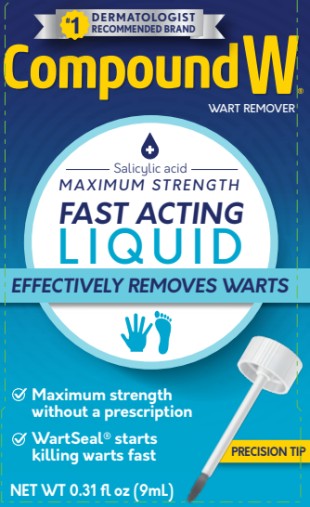 DRUG LABEL: Compound W
NDC: 63029-592 | Form: LIQUID
Manufacturer: Medtech Products Inc.
Category: otc | Type: HUMAN OTC DRUG LABEL
Date: 20250808

ACTIVE INGREDIENTS: SALICYLIC ACID 0.17 g/9 g
INACTIVE INGREDIENTS: ALCOHOL; CAMPHOR, (-)-; CASTOR OIL; LYTTA VESICATORIA; ETHER; ETHYLCELLULOSES; HYPOPHOSPHOROUS ACID; MENTHOL, (+)-; POLYSORBATE 80

Compound W Liquid 63029-592

Compound W®

Salicylic Acid LIQUID

NET WT 0.31 FL OZ (9 mL)

Drug Facts

Purpose

Salicylic acid 17% w/w............................................... Wart remover

Use

- for the removal of common and plantar warts
- the common wart is easily recognized by the rough “cauliflower-like” appearance of the surface
- the plantar wart is recognized by its location only on the bottom of the foot, its tenderness and the interruption of the footprint pattern

Warnings

For external use only.

Flammable. Keep aware from fire and flame.

Do not use

- on irritated skin or on any area that is infected or reddened
- on moles, birthmarks, warts with hair growing from them, genital warts or warts on the face or mucous membranes
- if you have diabetes or poor blood circulation

When using this product

- avoid contact with eyes. If product gets into the eye, flush with water for 15 minutes
- avoid inhaling vapors
- Cap bottle tightly and store at room temperature away from heat

Keep out of reach of children.

If swallowed, get medical help or contact a Poison Control Center (1-800-222-1222) right away.

Directions

• wash affected area

• may soak wart in warm water for 5 minutes

• dry area thoroughly

• using applicator, apply one drop at a time to sufficiently cover each wart

• let dry

• repeat this procedure once or twice daily as needed (until wart is removed) for up to 12 weeks

Other Information

- store at room temperature
- avoid excessive heat 37C (99F)
- skin discoloration may occur during or after use
- wipe the rim of the bottle with a paper towel between uses

Inactive ingredients

alcohol, camphor, castor oil, collodion, ether, ethylcellulose, hypophosphorous acid, menthol, polysorbate 80

Questions?

1-800-443-4908 Compoundw.com

PRINCIPAL DISPLAY PANEL

CompoundW
Salicylic Acid Liquid
NetWT 0.31 fl oz (9mL)